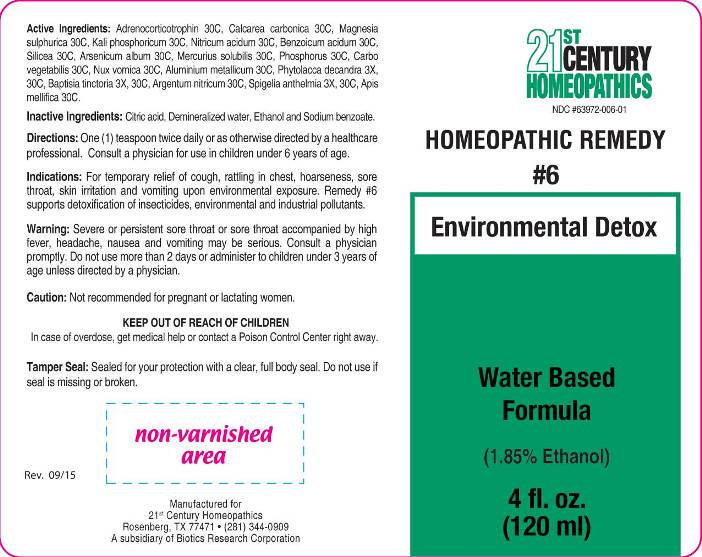 DRUG LABEL: 6 Environmental Detox
NDC: 63972-006 | Form: LIQUID
Manufacturer: 21st Century Homeopathics, Inc
Category: homeopathic | Type: HUMAN OTC DRUG LABEL
Date: 20150928

ACTIVE INGREDIENTS: BAPTISIA TINCTORIA ROOT 3 [hp_X]/1 mL; PHYTOLACCA AMERICANA ROOT 3 [hp_X]/1 mL; SPIGELIA ANTHELMIA 3 [hp_X]/1 mL; CORTICOTROPIN 30 [hp_C]/1 mL; ALUMINUM 30 [hp_C]/1 mL; APIS MELLIFERA 30 [hp_C]/1 mL; SILVER NITRATE 30 [hp_C]/1 mL; ARSENIC TRIOXIDE 30 [hp_C]/1 mL; BENZOIC ACID 30 [hp_C]/1 mL; OYSTER SHELL CALCIUM CARBONATE, CRUDE 30 [hp_C]/1 mL; ACTIVATED CHARCOAL 30 [hp_C]/1 mL; POTASSIUM PHOSPHATE, DIBASIC 30 [hp_C]/1 mL; MAGNESIUM SULFATE HEPTAHYDRATE 30 [hp_C]/1 mL; MERCURIUS SOLUBILIS 30 [hp_C]/1 mL; NITRIC ACID 30 [hp_C]/1 mL; STRYCHNOS NUX-VOMICA SEED 30 [hp_C]/1 mL; PHOSPHORUS 30 [hp_C]/1 mL; SILICON DIOXIDE 30 [hp_C]/1 mL
INACTIVE INGREDIENTS: CITRIC ACID MONOHYDRATE; WATER; ALCOHOL; SODIUM BENZOATE

ACTIVE INGREDIENTS:

Adrenocorticotrophin 30C, Calcarea carbonica 30C, Magnesia sulphurica 30C, Kali phosphoricum 30C, Nitricum acidum 30C, Benzoicum acidum 30C, Silicea 30C, Arsenicum album 30C, Mercurius solubilis 30C, Phosphorus 30C, Carbo vegetabilis 30C, Nux vomica 30C, Aluminum metallicum 30C, Phytolacca decandra 3X,30C, Baptisia tinctoria 3X,30C, Argentum nitricum 30C, Spigelia anthelmia 3X, 30C, Apis mellifica 30C.

INDICATIONS:

For temporary relief of cough, rattling in chest, hoarseness, sore throat, skin irritation and vomiting upon environmental exposure. Remedy # 6 supports detoxification of insecticides, environmental and industrial pollutants.

WARNINGS:

Severe or persistant sore throat or sore throat accompanied by high fever, headache, nausea and vomiting may be serious. Consult a physician promptly. Do not use more than 2 days or administer to children under 3 years of age unless directed by a physician.

Caution: Not recommended for pregnant or lactating women.

KEEP OUT OF REACH OF CHILDREN:

In case of overdose, get medical help or contact a Poison Control Center right away.

DIRECTIONS:

One (1) teaspoon twice daily or as otherwise directed by a healthcare professional.
Consult a physician for use in children under 6 years of age.

INDICATIONS:

For temporary relief of cough, rattling in chest, hoarseness, sore throat, skin irritation and vomiting upon environmental exposure. Remedy # 6 supports detoxification of insecticides, environmental and industrial pollutants.

INACTIVE INGREDIENTS:

Citric Acid, Demineralized Water, Ethanol 2.1%, Sodium Benzoate.

QUESTIONS:

Manufactured for

21st Century Homeopathics

Rosenberg, TX 77471 (281) 344-0909

A subsidiary of Biotics Research Corporation

PACKAGE LABEL

21st CENTURY

HOMEOPATHICS

HOMEOPATHIC REMEDY

#6

Environmental Detox

Water Based

Formula

4 fl. oz.

(120ml)